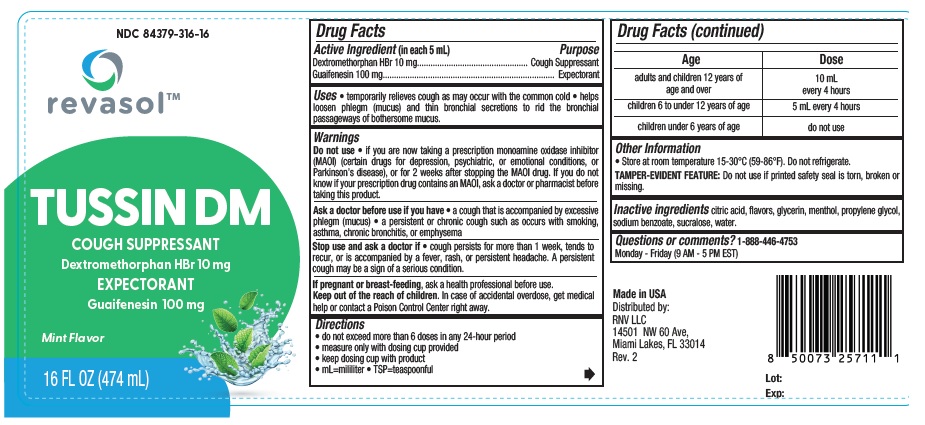 DRUG LABEL: Revasol Tussin DM Cough Suppressant Expectorant
NDC: 84379-316 | Form: LIQUID
Manufacturer: Rnv LLC
Category: otc | Type: HUMAN OTC DRUG LABEL
Date: 20260223

ACTIVE INGREDIENTS: DEXTROMETHORPHAN HYDROBROMIDE 10 mg/5 mL; GUAIFENESIN 100 mg/5 mL
INACTIVE INGREDIENTS: SODIUM BENZOATE; ANHYDROUS CITRIC ACID; GLYCERIN; MENTHOL; XANTHAN GUM; SUCRALOSE; PROPYLENE GLYCOL; WATER

Revasol Tussin DM Cough Suppressant Expectorant NDC 84379-316-16

ACTIVE INGREDIENT

Dextromethorphan HBr 10 mg
Guaifenesin 100 mg

PURPOSE

Cough Suppressant

Expectorant

INDICATIONS AND USAGE

Uses • temporarily relieves cough as may occur with the common cold • helps
loosen phlegm (mucus) and thin bronchial secretions to rid the bronchial
passageways of bothersome mucus.

Warnings

Do not use • if you are now taking a prescription monoamine oxidase inhibitor
(MAOI) (certain drugs for depression, psychiatric, or emotional conditions, or
Parkinson’s disease), or for 2 weeks after stopping the MAOI drug. If you do not
know if your prescription drug contains an MAOI, ask a doctor or pharmacist before
taking this product.

Ask a doctor before use if you have • a cough that is accompanied by excessive
phlegm (mucus) • a persistent or chronic cough such as occurs with smoking,
asthma, chronic bronchitis, or emphysema

Stop use and ask a doctor if • cough persists for more than 1 week, tends to
recur, or is accompanied by a fever, rash, or persistent headache. A persistent
cough may be a sign of a serious condition.

PREGNANCY OR BREAST FEEDING

If pregnant or breast-feeding, ask a health professional before use.

KEEP OUT OF REACH OF CHILDREN

Keep out of the reach of children. In case of accidental overdose, get medical
help or contact a Poison Control Center right away.

Directions
• do not exceed more than 6 doses in any 24-hour period
• measure only with dosing cup provided
• keep dosing cup with product
• mL=mililiter • TSP=teaspoonful

Age | Dose
adults and children 12 years of age and over | 10 mL every 4 hours
children 6 to under 12 years of age | 5 mL every 4 hours
children under 6 years of age | do not use

Other Information

• Store at room temperature 15-30°C (59-86°F). Do not refrigerate.
TAMPER-EVIDENT FEATURE: Do not use if printed safety seal is torn, broken or missing.

INACTIVE INGREDIENT

Inactive ingredients citric acid, flavors, glycerin, menthol, propylene glycol,
sodium benzoate, sucralose, water.

Questions or comments? 1-888-446-4753
Monday - Friday (9 AM - 5 PM EST)

Made in USA

Distributed by:
RNV LLC
14501 NW 60 Ave,
Miami Lakes, FL 33014